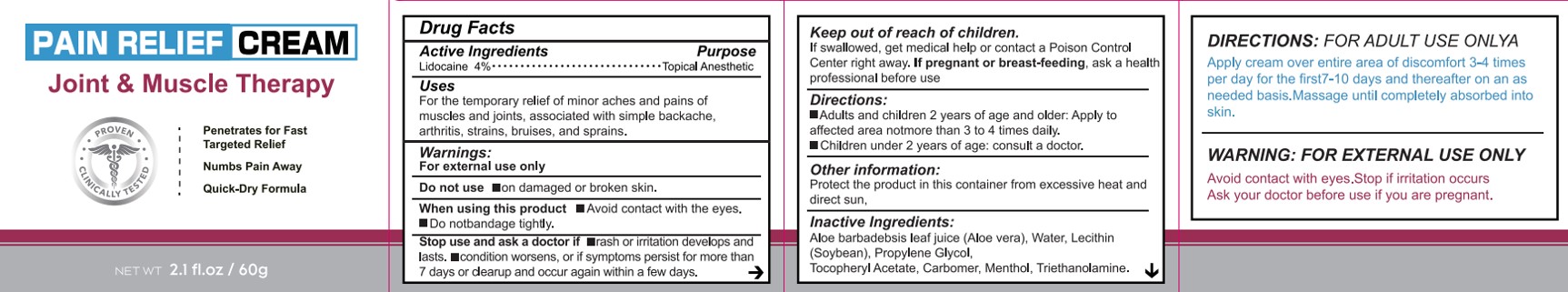 DRUG LABEL: Pain Relief Cream
NDC: 84023-301 | Form: PASTE
Manufacturer: Shenzhen Yangan Technology Co., Ltd.
Category: otc | Type: HUMAN OTC DRUG LABEL
Date: 20240130

ACTIVE INGREDIENTS: LIDOCAINE 4 g/100 g
INACTIVE INGREDIENTS: LECITHIN, SOYBEAN; ALOE; WATER; PROPYLENE GLYCOL; ALPHA-TOCOPHEROL ACETATE; MENTHOL; CARBOMER HOMOPOLYMER, UNSPECIFIED TYPE; TROLAMINE

Pain Relief Cream

Pain Relief Cream

ACTIVE INGREDIENT

Lidocaine 4%

PURPOSE

Topical Anesthetic

INDICATIONS AND USAGE

For the temporary relief of minor aches and pains of muscles and joints, associated with simple backache, arthritis, strains, bruises, and sprains.

WARNINGS

For external use only

DO NOT USE

on damaged or broken skin.

WHEN USING

Avoid contact with the eyes.
Do notbandage tightly.

STOP USE

rash or irritation develops and lasts.
condition worsens, or if symptoms persist for more than 7 days or dearup and occur again within a few days.

KEEP OUT OF REACH OF CHILDREN

If swallowed, get medical help or contact a Poison Control Center right away. If pregnant or breast-feeding, ask a health professional before use

DOSAGE AND ADMINISTRATION

Adults and children 2 years of age and older: Apply to affected area notmore than 3 to 4 times daily.
Children under 2 years of age: consult a doctor.

STORAGE AND HANDLING

Protect the product in this container from excessive heat and direct sun.

INACTIVE INGREDIENT

Aloe barbadebsis leaf juice (Aloe vera)
Water
Lecithin (Soybean)
Propylene Glycol
Tocopheryl Acetate
Carbomer
Menthol
Triethanolamine